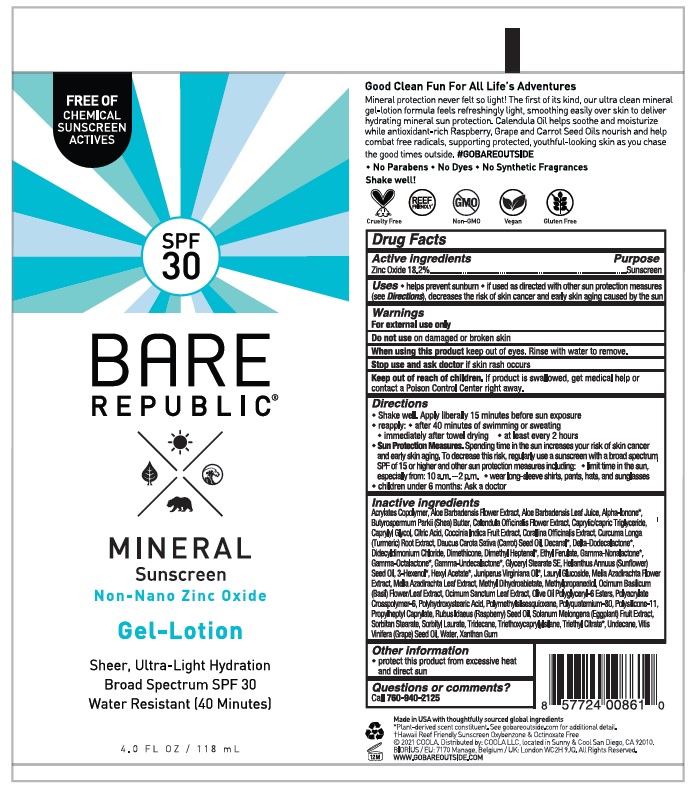 DRUG LABEL: Coola Bare Republic Mineral Body Gel-Lotion
NDC: 79753-042 | Form: LOTION
Manufacturer: COOLA LLC
Category: otc | Type: HUMAN OTC DRUG LABEL
Date: 20231220

ACTIVE INGREDIENTS: ZINC OXIDE 18.2 g/100 mL
INACTIVE INGREDIENTS: BUTYL ACRYLATE/METHYL METHACRYLATE/METHACRYLIC ACID COPOLYMER (18000 MW); ALOE VERA FLOWER; ALOE VERA LEAF; .ALPHA.-IONONE; SHEA BUTTER; CALENDULA OFFICINALIS FLOWER; MEDIUM-CHAIN TRIGLYCERIDES; CAPRYLYL GLYCOL; CITRIC ACID MONOHYDRATE; COCCINIA GRANDIS FRUIT; CORALLINA OFFICINALIS; TURMERIC; CARROT SEED OIL; DECANAL; .DELTA.-DODECALACTONE; DIDECYLDIMONIUM CHLORIDE; DIMETHICONE; 2,6-DIMETHYL-5-HEPTENAL; ETHYL FERULATE; .GAMMA.-NONALACTONE; .GAMMA.-OCTALACTONE; .GAMMA.-UNDECALACTONE; GLYCERYL STEARATE SE; SUNFLOWER OIL; 3-HEXEN-1-OL, (3Z)-; HEXYL ACETATE; JUNIPERUS VIRGINIANA OIL; LAURYL GLUCOSIDE; AZADIRACHTA INDICA FLOWER; AZADIRACHTA INDICA LEAF; METHYL DIHYDROABIETATE; METHYLPROPANEDIOL; OCIMUM BASILICUM FLOWERING TOP; HOLY BASIL LEAF; OLIVE OIL POLYGLYCERYL-6 ESTERS; AMMONIUM ACRYLOYLDIMETHYLTAURATE, DIMETHYLACRYLAMIDE, LAURYL METHACRYLATE AND LAURETH-4 METHACRYLATE COPOLYMER, TRIMETHYLOLPROPANE TRIACRYLATE CROSSLINKED (45000 MPA.S); POLYHYDROXYSTEARIC ACID (2300 MW); POLYMETHYLSILSESQUIOXANE (4.5 MICRONS); DIMETHICONE/VINYL DIMETHICONE CROSSPOLYMER (SOFT PARTICLE); PROPYLHEPTYL CAPRYLATE; RASPBERRY SEED OIL; EGGPLANT; SORBITAN MONOSTEARATE; SORBITYL LAURATE; TRIDECANE; TRIETHOXYCAPRYLYLSILANE; TRIETHYL CITRATE; UNDECANE; GRAPE SEED OIL; WATER; XANTHAN GUM

Coola Bare Republic Mineral Body Gel Lotion SPF 30

Drug Facts

Active Ingredients

Zinc Oxide 18.2%

Purpose

Suncreen

INDICATIONS AND USAGE

Uses • helps prevent sunburn • if used as directed with other sun protection measures

(see Directions), decreases the risk of skin cancer and early skin aging caused by the sun

Warnings

For external use only

Do not use on damaged or broken skin

When using this product keep out of eyes. Rinse with water to remove.

Stop use and ask doctor if skin rash occurs

Keep out of reach of children. If product is swallowed, get medical help or

contact a Poison Control Center right away.

Directions
● Shake well. Apply liberally 15 minutes before sun exposure
● reapply:
● after 40 minutes of swimming or sweating
● immediately after towel drying
● at least every 2 hours
● Sun Protection Measures. Spending time in the sun
increases your risk of skin cancer and early skin aging. To
decrease this risk, regularly use a sunscreen with a broad
spectrum SPF of 15 or higher and other sun protection
measures including:
● limit time in the sun, especially from:
10 a.m. - 2 p.m.
● wear long-sleeve shirts, pants, hats, and sunglasses
● Children under 6 months: Ask a doctor

Inactive Ingredients
Acrylates Copolymer, Aloe Barbadensis Flower Extract, Aloe Barbadensis Leaf Juice, Alpha-Ionone*,
Butyrospermum Parkii (Shea) Butter, Calendula Officinalis Flower Extract, Caprylic/capric Triglyceride,
Caprylyl Glycol, Citric Acid, Coccinia Indica Fruit Extract, Corallina Officinalis Extract, Curcuma Longa
(Turmeric) Root Extract, Daucus Carota Sativa (Carrot) Seed Oil, Decanal*, Delta-Dodecalactone*,
Didecyldimonium Chloride, Dimethicone, Dimethyl Heptenal*, Ethyl Ferulate, Gamma-Nonalactone*,
Gamma-Octalactone*, Gamma-Undecalactone*, Glyceryl Stearate SE, Helianthus Annuus (Sunflower)
Seed Oil, 3-Hexenol*, Hexyl Acetate*, Juniperus Virginiana Oil*, Lauryl Glucoside, Melia Azadirachta Flower
Extract, Melia Azadirachta Leaf Extract, Methyl Dihydroabietate, Methlypropanediol, Ocimum Basilicum
(Basil) Flower/Leaf Extract, Ocimum Sanctum Leaf Extract, Olive Oil Polyglyceryl-6 Esters, Polyacrylate
Crosspolymer-6, Polyhydroxystearic Acid, Polymethylsilsesquioxane, Polyquaternium-80, Polysilicone-11,
Propylheptyl Caprylate, Rubus Idaeus (Raspberry) Seed Oil, Solanum Melongena (Eggplant) Fruit Extract,
Sorbitan Stearate, Sorbityl Laurate, Tridecane, Triethoxycaprylylsilane, Triethyl Citrate*, Undecane, Vitis
Vinifera (Grape) Seed Oil, Water, Xanthan Gum

Other information

- protect this product from excessive heat and direct sun

Questions or comments?
Call 760-940-2125

COOLA Label

SPF

30

BARE

REPUBLIC

MINERAL

Sunscreen

Non-Nano Zinc Oxide

Gel-Lotion

Sheer, Ultra-Light Hydration

Broad Spectrum SPF 30

Water Resistant (40 Minutes)

4.0 FL OZ / 118 mL

*Hawaii Reef Friendly Sunscreen Oxybenzone & Octinoxate Free
©2021 COOLA. Distributed by: COOLA LLC, located in Sunny & Cool

San Diego, CA 92010.

WWW.GOBAREOUTSIDE.COM

res